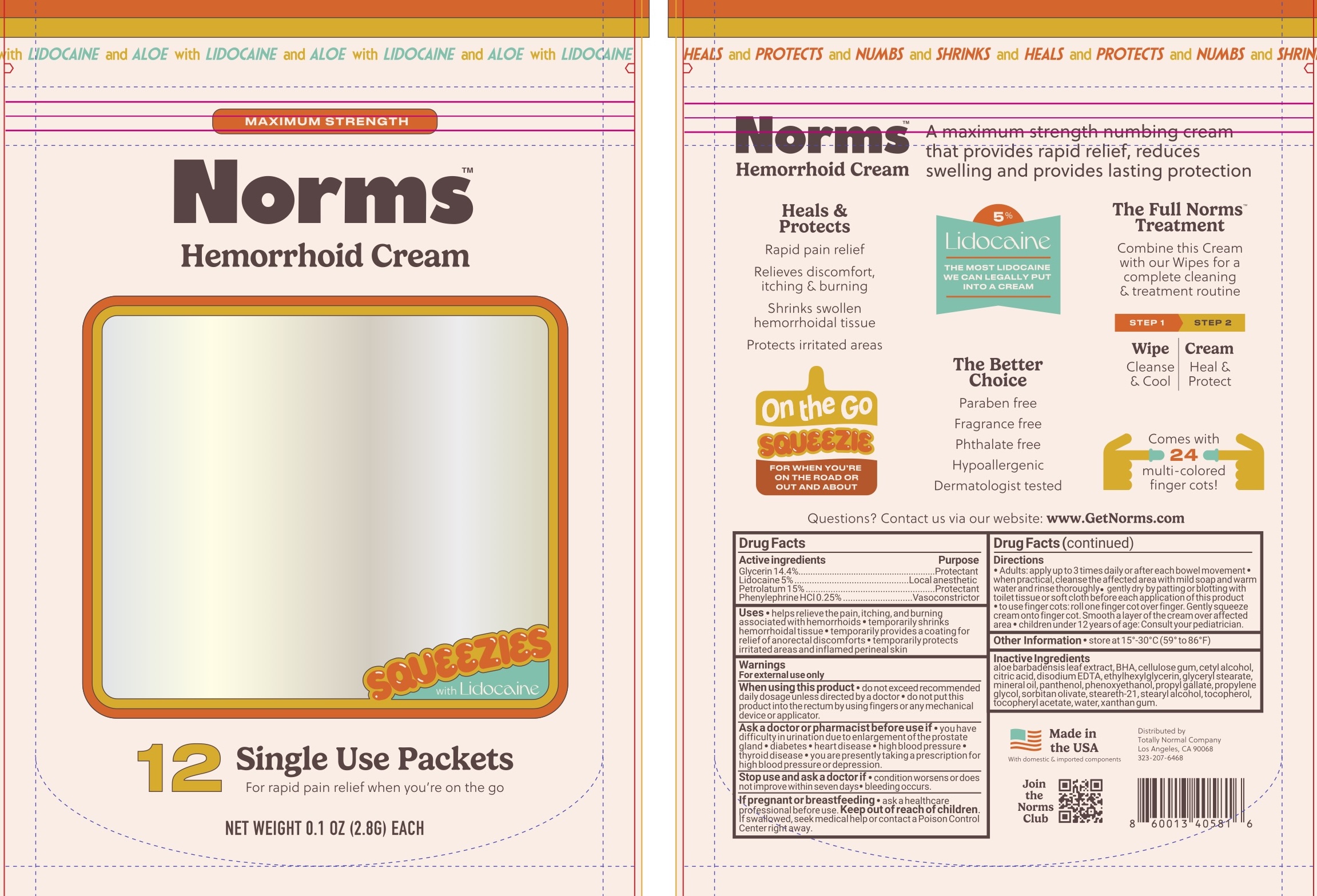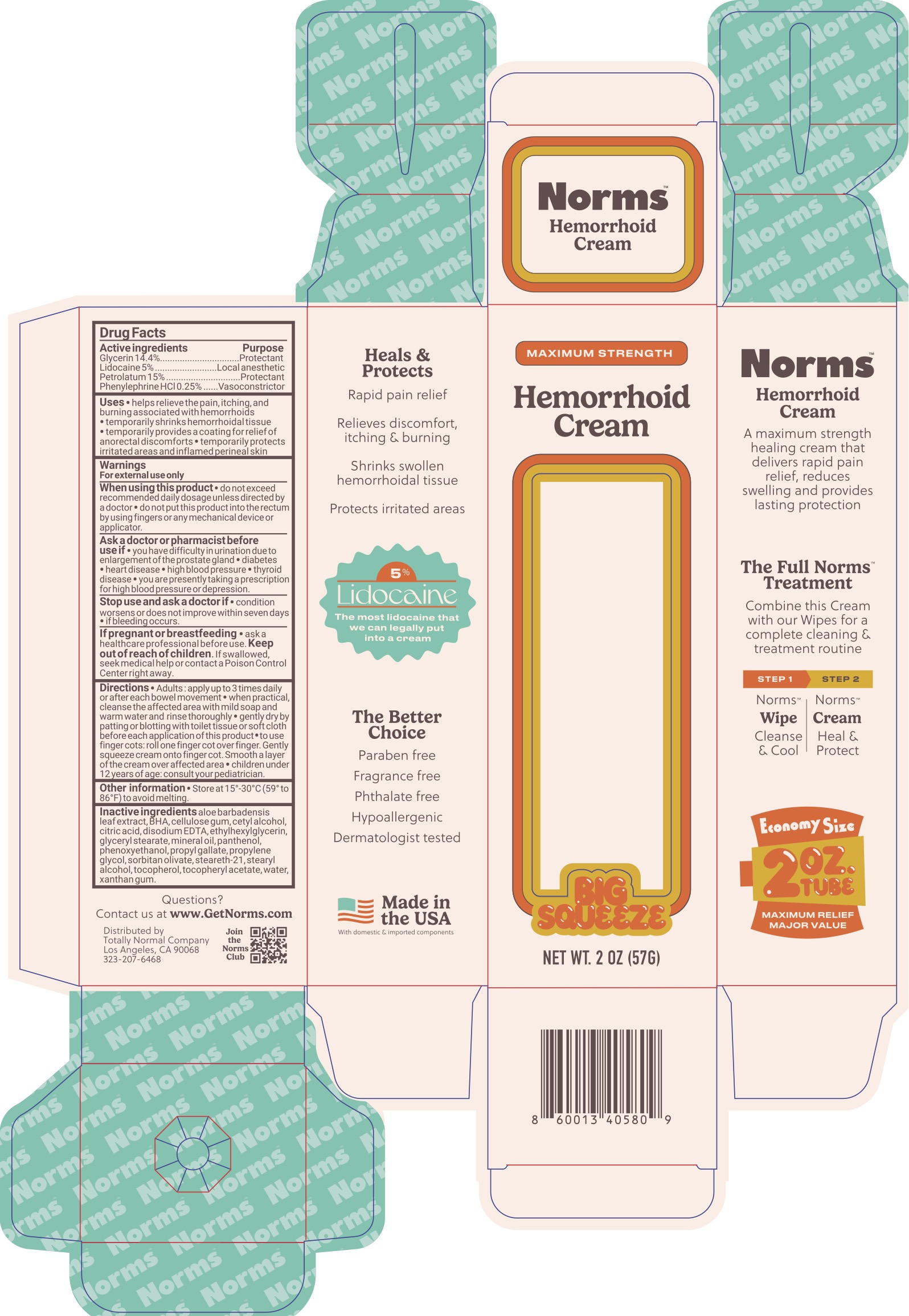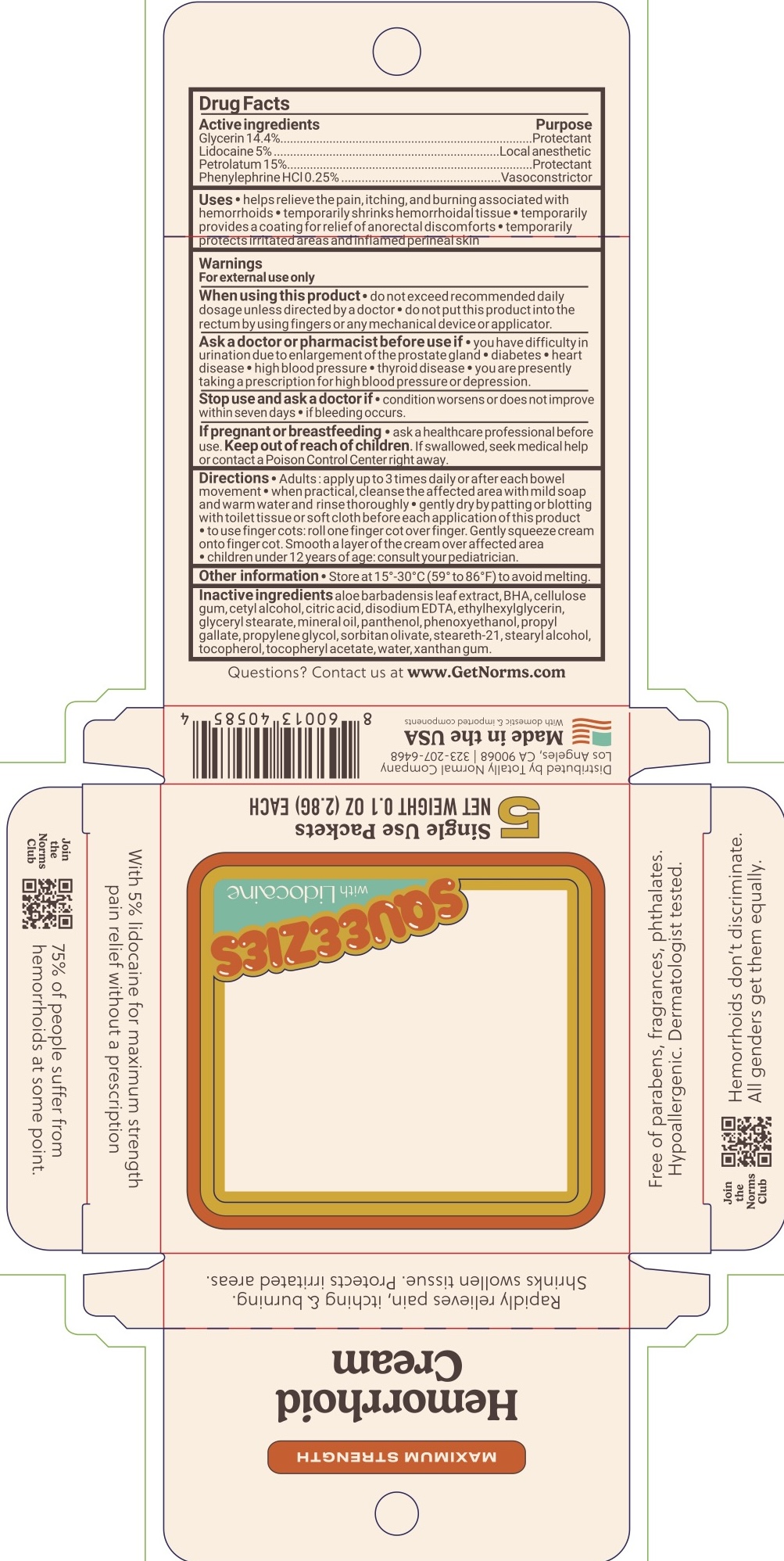 DRUG LABEL: Norms Hemorrhoid
NDC: 85996-173 | Form: CREAM
Manufacturer: Totally Normal Company
Category: otc | Type: HUMAN OTC DRUG LABEL
Date: 20250808

ACTIVE INGREDIENTS: LIDOCAINE 5 g/100 g; PETROLATUM 15 g/100 g; GLYCERIN 14.4 g/100 g; PHENYLEPHRINE HYDROCHLORIDE 0.25 g/100 g
INACTIVE INGREDIENTS: PHENOXYETHANOL; .ALPHA.-TOCOPHEROL ACETATE; XANTHAN GUM; CETYL ALCOHOL; CITRIC ACID MONOHYDRATE; EDETATE DISODIUM; PANTHENOL; BUTYLATED HYDROXYANISOLE; ALOE VERA LEAF; SORBITAN OLIVATE; STEARETH-21; WATER; ETHYLHEXYLGLYCERIN; GLYCERYL MONOSTEARATE; PROPYL GALLATE; PROPYLENE GLYCOL; CARBOXYMETHYLCELLULOSE SODIUM; STEARYL ALCOHOL; TOCOPHEROL; MINERAL OIL

Norms Hemorrhoidal Cream

ACTIVE INGREDIENT

Glycerin 14.4%, Lidocaine 5%, Petrolatum 15%, Phenylephrine HCl 0.25%

PURPOSE

Anorectal/Hemorrhoidal

INDICATIONS AND USAGE

Helps relieve the pain, itching, and burning associated with hemorrhoids. Temporarily shrinks hemorrhoidal tissue. Temporarily provides a coating for relief of anorectal discomforts. Temporarily protects irritated areas and inflamed perineal skin.

WARNINGS

For external use only.

When using this product do not exceed recommended dosage unless directed by a doctor, do not put this product into rectum by using fingers or any mechanical device or applicator.

Ask a doctor or pharmacist before use if you have difficulty in urination due to enlargement of the prostate gland, diabetes, heart disease, high blood pressure, thyroid disease, or you are presently taking a prescription for high blood pressure or depression.

Stop use and ask a doctor if condition worsens or does not improve within seven days, if bleeding occurs.

PREGNANCY OR BREAST FEEDING

Ask a health care professional before use.

KEEP OUT OF REACH OF CHILDREN

If swallowed, seek medical help or contact a Poison Control Center right away.

DOSAGE AND ADMINISTRATION

Adults: apply up to 3 times daily or after each bowl movement. When practical, cleanse the affected area with mild soap and warm water and rinse thoroughly. Gently dry by patting or blotting with toilet tissue or soft cloth before each application of this product. To use finger gots: roll one finger cot over finger. Gently squeeze cream onto finger cot. Smooth a layer of the cream over affected area.

Children under 12 years of age: consult your pediatrician.

INACTIVE INGREDIENT

Aloe barbadensis leaf extract, BHA, cellulose gum, cetyl alcohol, citric acid, disodium EDTA, ethylhexylglycerin, glyceryl stearate, mineral oil, panthenol, Phenoxyethanol, propyl gallate, propylene glycol, sorbitan olivate, steareth-21, stearyl alcohol, tocopherol, tocopheryl acetate, water, xanthan gum.